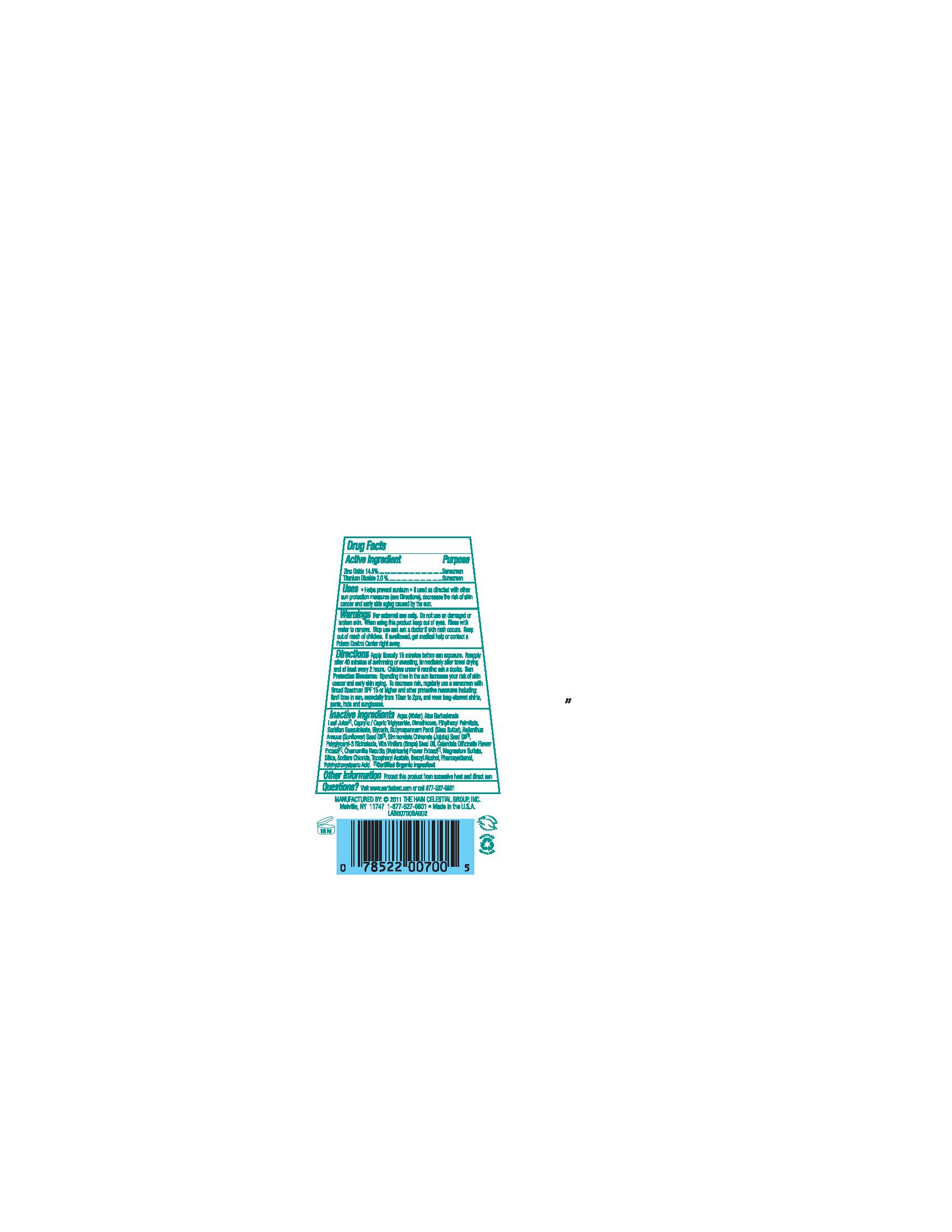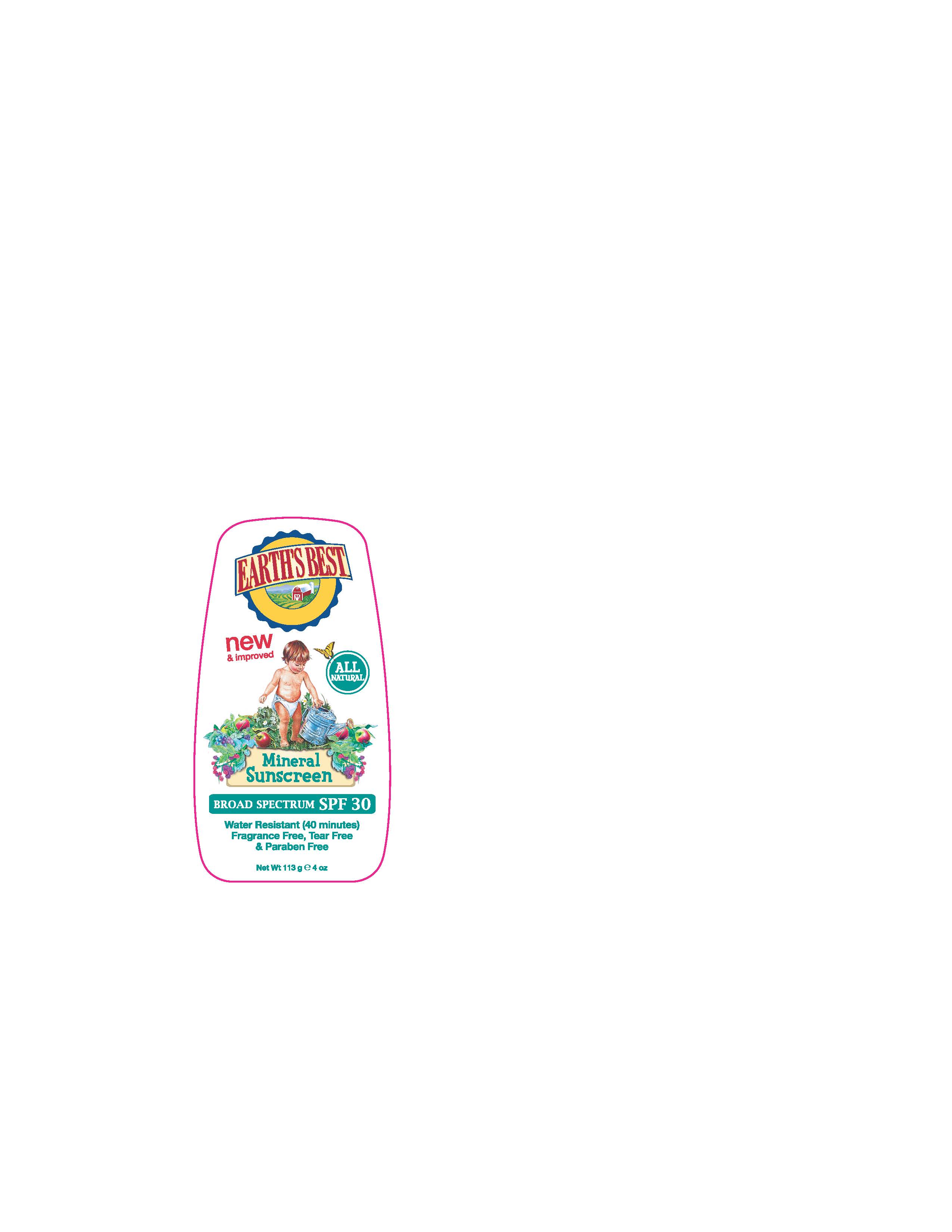 DRUG LABEL: Earths Best Mineral Sunscreen Broad Spectrum SPF30
NDC: 61995-0212 | Form: LOTION
Manufacturer: The Hain Celestial Group, Inc.
Category: otc | Type: HUMAN OTC DRUG LABEL
Date: 20120525

ACTIVE INGREDIENTS: ZINC OXIDE 14.5 g/100 g; TITANIUM DIOXIDE  2.0 g/100 g
INACTIVE INGREDIENTS: WATER; MEDIUM-CHAIN TRIGLYCERIDES; GLYCERIN; ALOE VERA LEAF; SUNFLOWER OIL ; DIMETHICONE; JOJOBA OIL; ETHYLHEXYL PALMITATE; SORBITAN SESQUIOLEATE ; SHEA BUTTER; GRAPE SEED OIL; CALENDULA OFFICINALIS FLOWER; CHAMOMILE ; MAGNESIUM SULFATE ; SILICON DIOXIDE ; SODIUM CHLORIDE; .ALPHA.-TOCOPHEROL ACETATE; BENZYL ALCOHOL; PHENOXYETHANOL; POLYHYDROXYSTEARIC ACID (2300 MW)

Drug Facts

ACTIVE INGREDIENT

Zinc Oxide 14.5%

Titanium Dioxide 2.0%

PURPOSE

Sunscreen

INDICATIONS AND USAGE

- Helps prevent sunburns
- If used as described with other sun protection measures, decreases the risk of skin cancer and early skin aging, caused by the sun.

WARNINGS

For external use only. Do not use on damaged or broken skin. When using this product keep out of eyes.Rinse with water to remove. Stop use and ask a doctor if skin rash occurs.

Keep out of reach of children. If swallowed, get medical help or contact a Poison Control Center right away.

DOSAGE AND ADMINISTRATION

Apply liberally 15 minutes before sun exposure. Reapply after 40 minutes of swimming or sweating, immediately after towel drying and at least every 2 hours. Children under 6 months, ask a doctor . Skin Protection Measures: Spending time in the sun increases your risk of skin cancer and early skin aging.To decrease risk, regularly use a sunscreen with Broad Spectrum SPF 15 or higher and other protective measures including: limit time in the sun, especially from 10am to 2pm and wear long-sleeved shirts, pants, hats and sunglasses.

INACTIVE INGREDIENT

Aqua (Water), Aloe Barbadensis Leaf Juice (1), Caprylic/Capric Triglycerides, Dimethicone, Ethylhexyl Palmitate, Sorbitan Sesquioleate, Glycerin, Butyrospermum Parkii (Shea Butter), Helianthus Annuus (Sunflower) Seed Oil (1), Simmondsia Chinensis (Jojoba) Seed Oil (1), Polyglyceryl-3 Ricinoleate, Vitis Vinifera (Grape) Seed) Oil, Calendula Officinalis Flower Extract (1),Chamomilla Recutita (Matricaria) Flower Extract (1), Magnesium Sulfate, Silica, Sodium Chloride,Tocopheryl Acetate, Benzyl Alcohol, Phenoxyethanol, Polyhydroxystearic Acid.

(1) Certified Organic Ingredients

QUESTIONS

Questions? Call (877) 527-6801or visit www.earthsbest.com